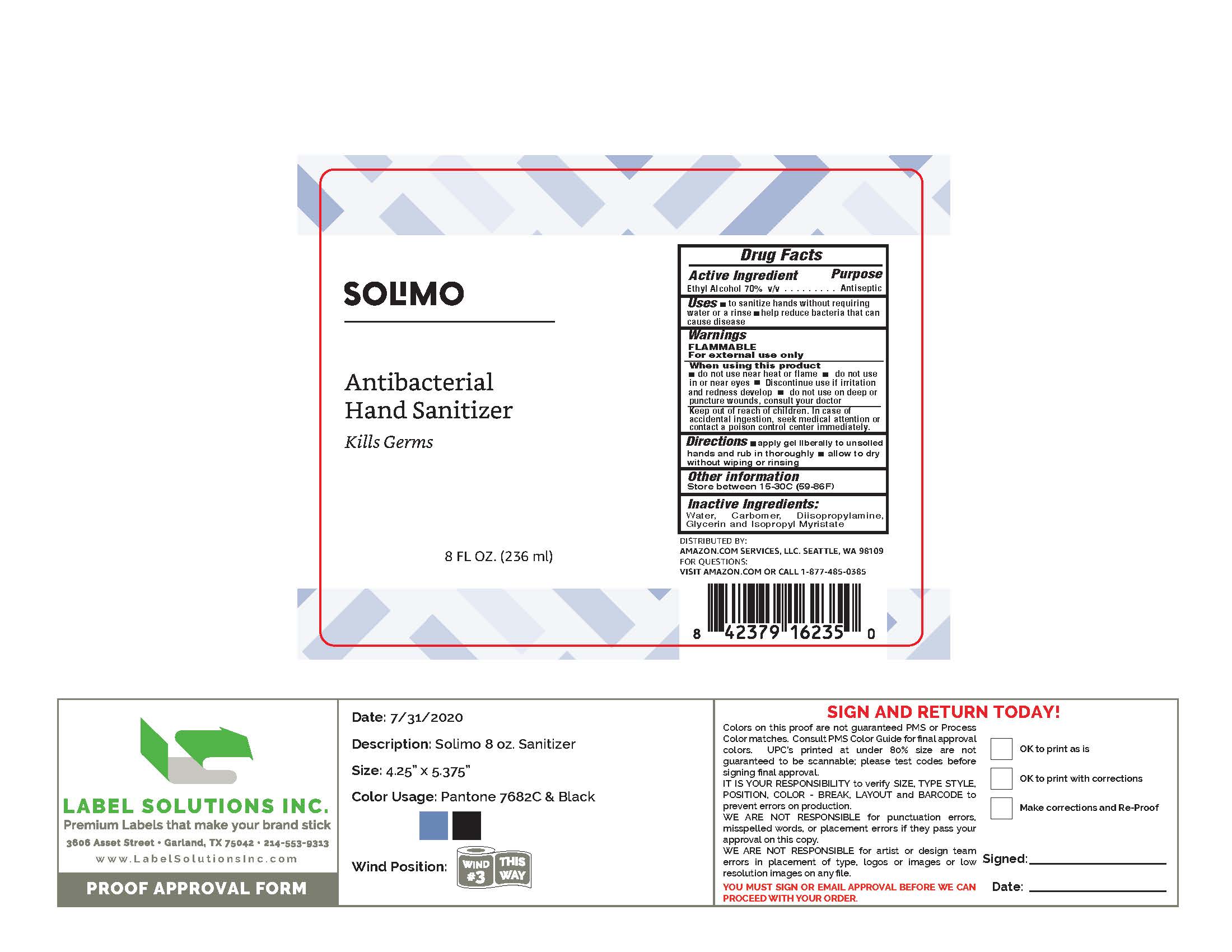 DRUG LABEL: Solimo
NDC: 72288-527 | Form: GEL
Manufacturer: Amazon.com Services LLC
Category: otc | Type: HUMAN OTC DRUG LABEL
Date: 20200902

ACTIVE INGREDIENTS: ALCOHOL 65.37 mL/100 mL
INACTIVE INGREDIENTS: DIISOPROPYLAMINE 0.174 mL/100 mL; WATER 33.78 mL/100 mL; CARBOMER HOMOPOLYMER, UNSPECIFIED TYPE 0.355 mL/100 mL; ISOPROPYL MYRISTATE 0.108 mL/100 mL; GLYCERIN 0.217 mL/100 mL

Solimo

Active ingredient

Ethyl Alcohol 70% v/v

Purpose

Antiseptic

Warnings

FLAMMABLE

For external use only

In case of accidental ingestion, seek medical attention or contact a poison control center immediately.

Directions

Apply gel liberally to unsoiled hands and rub in thoroughly.

Allow to dry without wiping or rinsing.

Other information

Store at room temperature

Inactive ingredients

Water, Carbomer, Glycerin, Diidopropylamine, Isopropyl Myristate.

Keep out of reach of children

When using this product

- do not use near heat or flame
- do not use in or near eyes
- discontinue use if irritation and redness develop
- do not use on deep or puncture wounds consulft your doctor

Uses

- to sanitizer hands without requiring water or a rinse
- help reduce bacteria that can cause disease